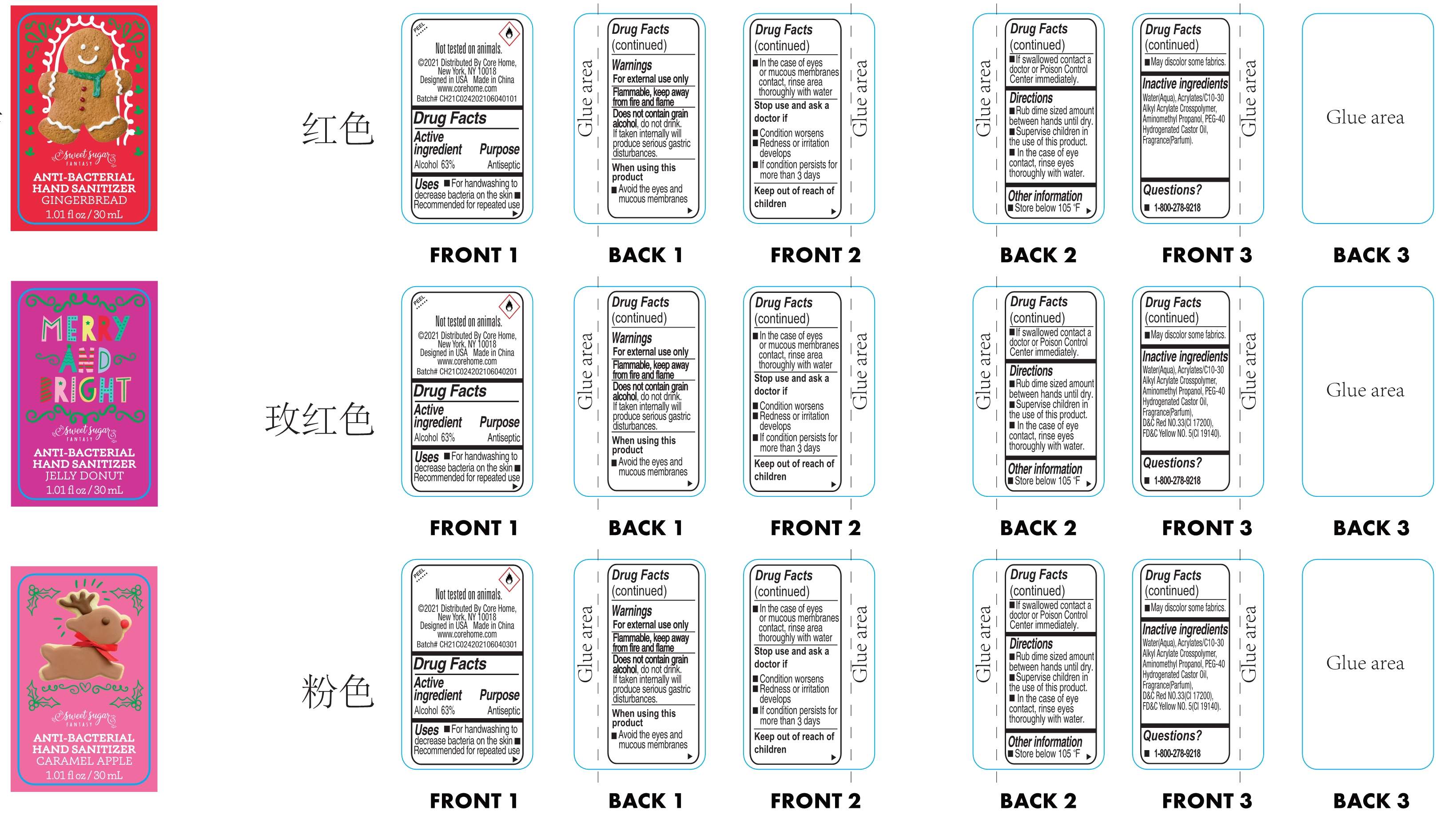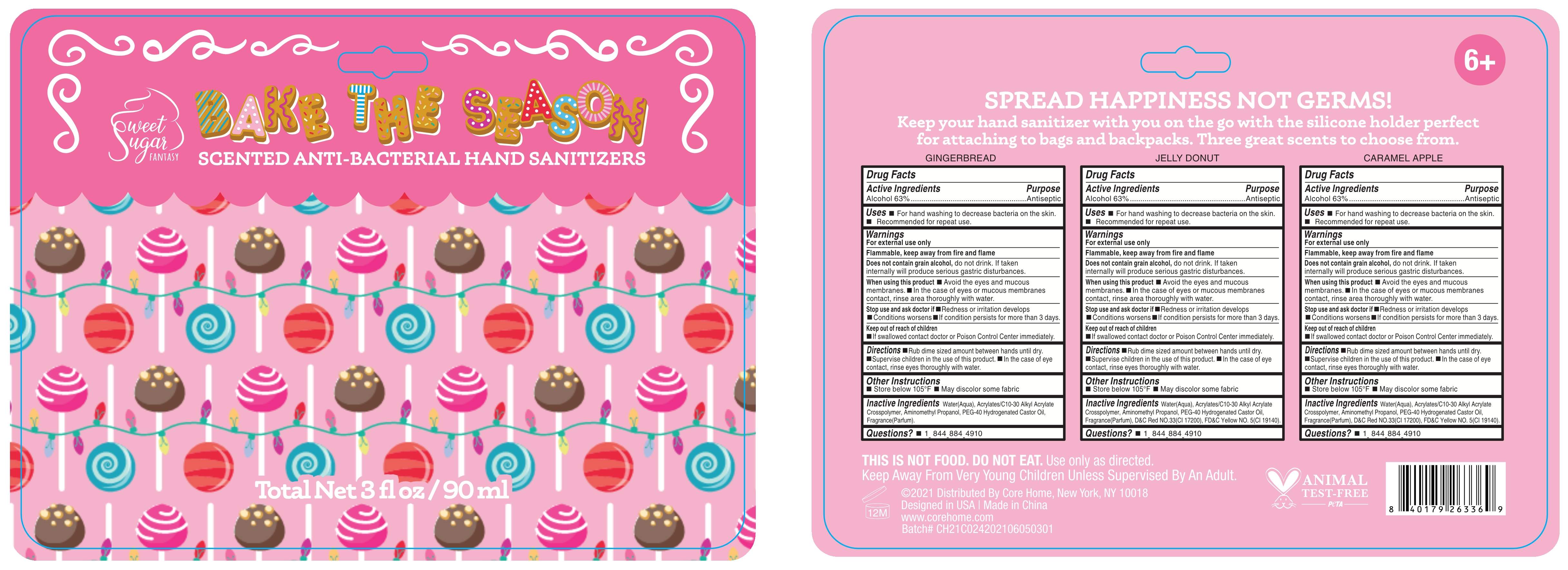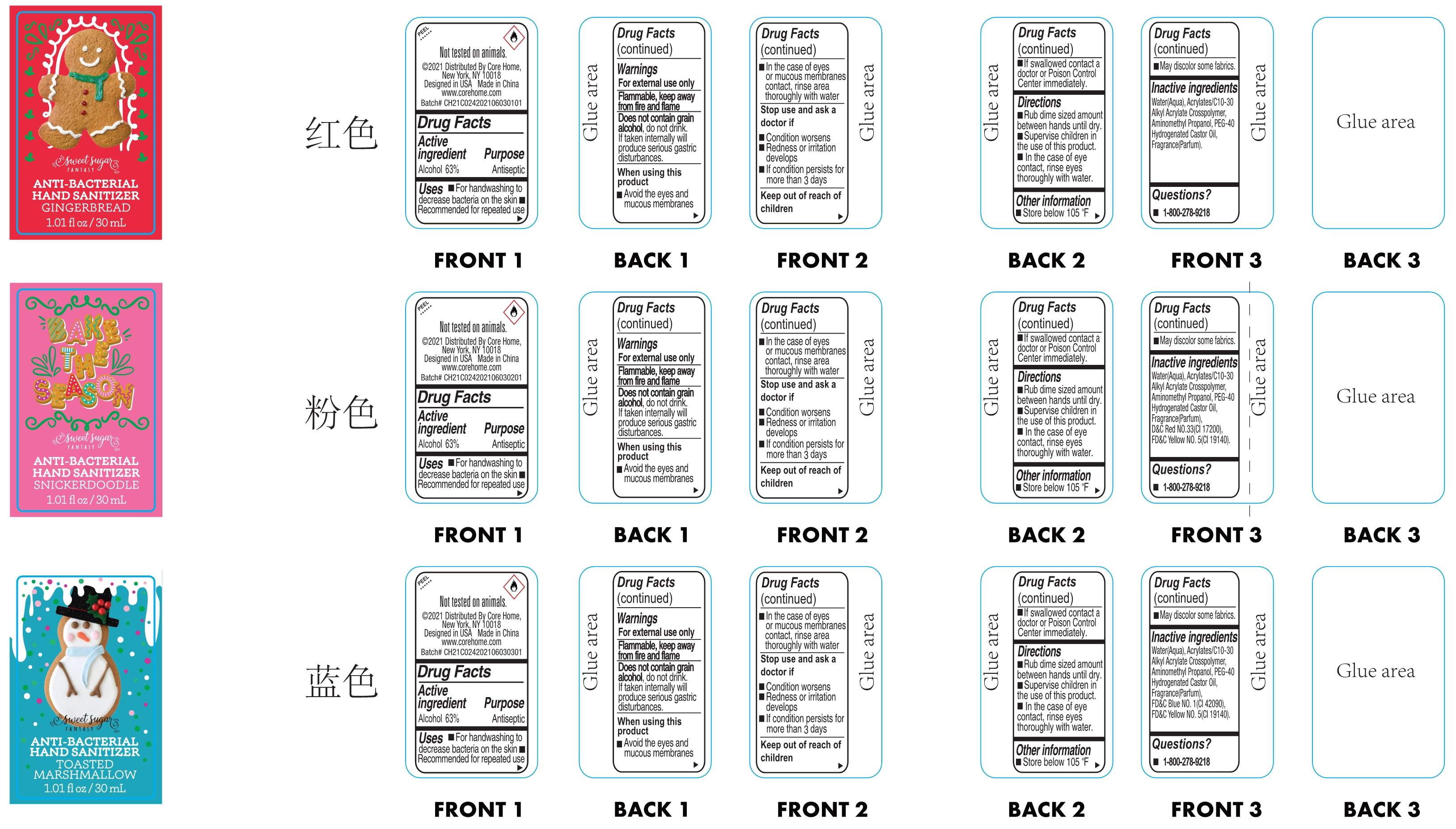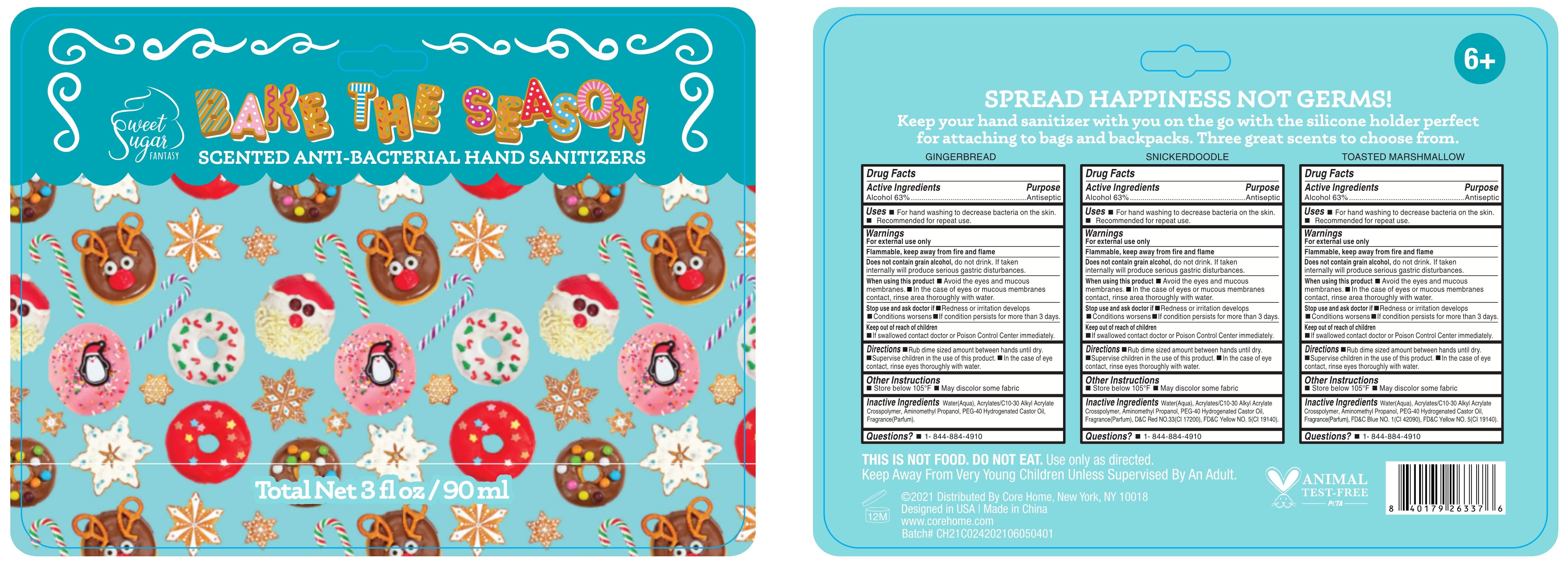 DRUG LABEL: SCENTED ANTI-BACTERIAL HAND SANITIZERS
NDC: 73549-014 | Form: GEL
Manufacturer: Fortress Expert Co., Ltd
Category: otc | Type: HUMAN OTC DRUG LABEL
Date: 20210523

ACTIVE INGREDIENTS: ALCOHOL 63 mL/100 mL
INACTIVE INGREDIENTS: POLYOXYL 40 HYDROGENATED CASTOR OIL; WATER; CARBOMER INTERPOLYMER TYPE A (ALLYL SUCROSE CROSSLINKED); AMINOMETHYLPROPANOL; FRAGRANCE CLEAN ORC0600327

73549-014
SCENTED ANTI-BACTERIAL HAND SANITIZERS

Active ingredient

Alcohol 63%.....Antiseptic

Purpose

Antiseptic

Use

■ For handwashing to decrease bacteria on the skin ■ Recommended for repeated use

Warnings

■ For external use only

■ Flammable, keep away from open flame and sources of heat

■ Does not contain grain alcohol; do not drink. If taken internally will produce gastric distrubances.

When using this product

■ Avoid the eyes and mucoous membranes

■ In the case of eyes or mucous membranes contacr, rinse area thoroughly with water

Stop use and ask a doctor if

■Redness or irritation develops
■Conditions worsens
■If condition persists for more than 3 days.

Keep out of reach of children

■ If swallowed, contact a doctor or Poison Control Center immediately

Directions

■ Rub dime sized amount between hands until dry.

■ Supervise children in the use of this product.

■ In the case of eye contact, rinse eyes thoroughly with water.

Other information

■ Store below 105ºF

■ May discolor some fabrics.

Inactive ingredients

Wate(Aqua), Acryates/C10-30 Akyl Acryae Crosspolymer, Aminomethyl Propanol, PEG-40 Hydrogenated Castor OiL, Fragrance(Parfum) .

Questions?

■ 1-844-884-4910

Package Label

73549-014-01 XZ21E100 30ML

73549-014-02 XZ21E100 90ML

73549-014-03 XZ21E101 30ML

73549-014-04 XZ21E101 90ML